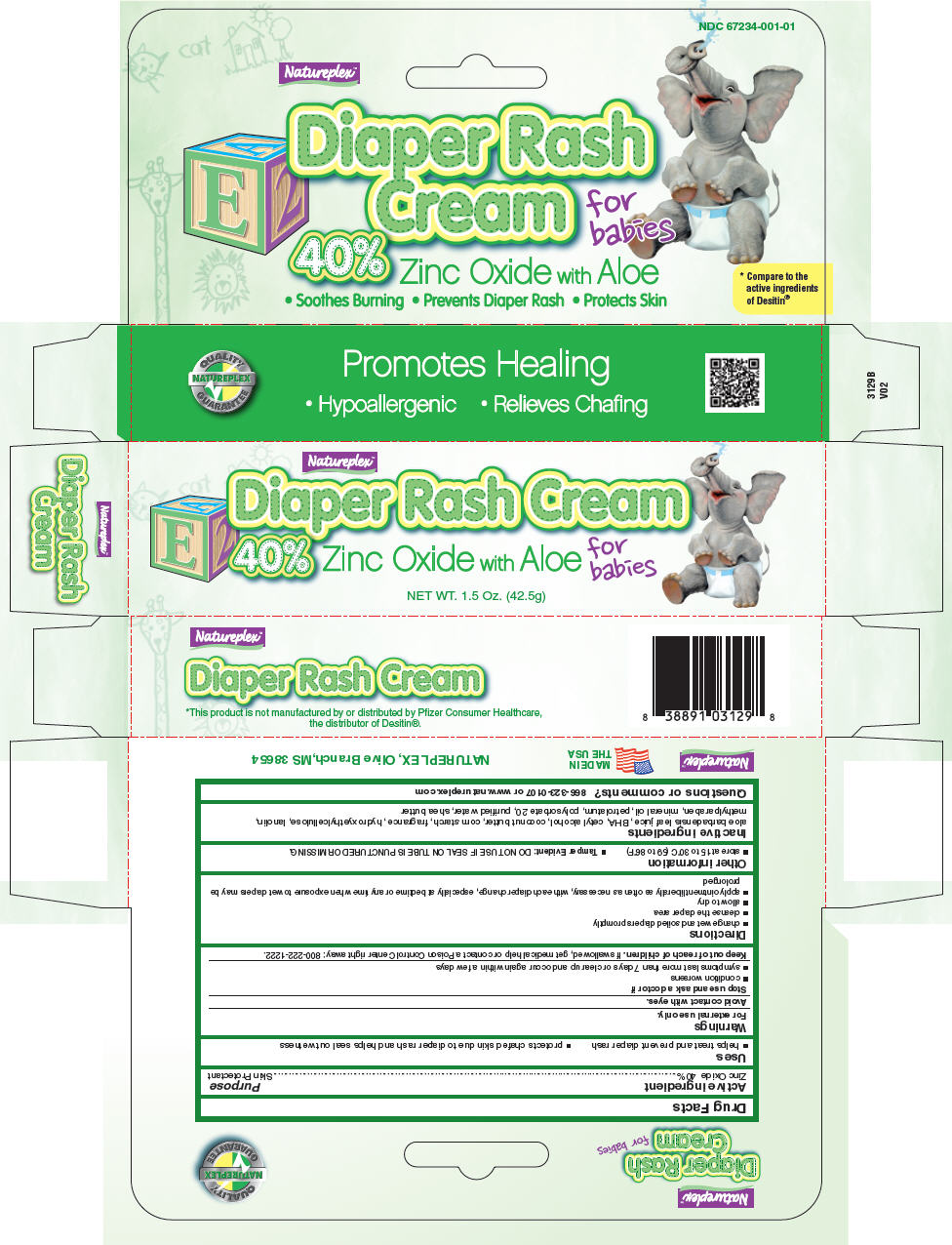 DRUG LABEL: Natureplex Diaper Rash
NDC: 67234-001 | Form: CREAM
Manufacturer: Natureplex LLC
Category: otc | Type: HUMAN OTC DRUG LABEL
Date: 20250815

ACTIVE INGREDIENTS: ZINC OXIDE 400 mg/1 g
INACTIVE INGREDIENTS: ALOE VERA LEAF; BUTYLATED HYDROXYANISOLE; CETYL ALCOHOL; COCOA BUTTER; STARCH, CORN; HYDROXYETHYL CELLULOSE (100 MPA.S AT 2%); LANOLIN; METHYLPARABEN; MINERAL OIL; PETROLATUM; POLYSORBATE 20; WATER; SHEA BUTTER

Natureplex™

Drug Facts

Active ingredient

Zinc Oxide 40%

Purpose

Skin Protectant

Uses

- helps treat and prevent diaper rash
- protects chafed skin due to diaper rash and helps seal out wetness

Warnings

For external use only.

Avoid contact with eyes.

Stop use and ask a doctor if

- condition worsens
- symptoms last more than 7 days or clear up and occur again within a few days

Keep out of reach of children. If swallowed, get medical help or contact a Poison Control Center right away: 800-222-1222.

Directions

- change wet and soiled diapers promptly
- cleanse the diaper area
- allow to dry
- apply ointment liberally as often as necessary, with each diaper change, especially at bedtime or any time when exposure to wet diapers may be prolonged

Other information

- store at 15 to 30°C (59 to 86°F)
- Tamper Evident: DO NOT USE IF SEAL ON TUBE IS PUNCTURED OR MISSING.

Inactive ingredients

aloe barbadensis leaf juice, BHA, cetyl alcohol, coconut butter, corn starch, fragrance, hydroxyethylcellulose, lanolin, methylparaben, mineral oil, petrolatum, polysorbate 20, purified water, shea butter

Questions or comments?

866-323-0107 or www.natureplex.com

PRINCIPAL DISPLAY PANEL - 42.5 g Tube Box

Natureplex™

Diaper Rash Cream
40% Zinc Oxide with Aloe
for
babies

NET WT. 1.5 Oz. (42.5g)